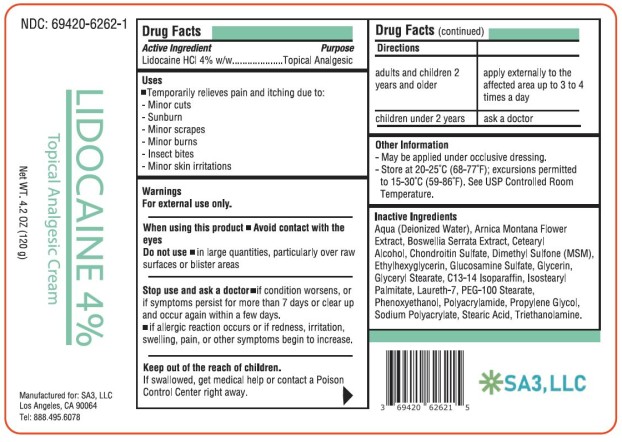 DRUG LABEL: Lidocaine 4 Percent
NDC: 69420-6262 | Form: CREAM
Manufacturer: SA3, LLC
Category: otc | Type: HUMAN OTC DRUG LABEL
Date: 20241209

ACTIVE INGREDIENTS: LIDOCAINE HYDROCHLORIDE 4 g/100 g
INACTIVE INGREDIENTS: WATER; ARNICA MONTANA FLOWER; INDIAN FRANKINCENSE; CETOSTEARYL ALCOHOL; ETHYLHEXYLGLYCERIN; GLUCOSAMINE SULFATE; GLYCERIN; GLYCERYL MONOSTEARATE; C13-14 ISOPARAFFIN; ISOSTEARYL PALMITATE; LAURETH-7; PEG-100 STEARATE; PHENOXYETHANOL; PROPYLENE GLYCOL; STEARIC ACID; TROLAMINE; CHONDROITIN SULFATE (BOVINE); DIMETHYL SULFONE; POLYACRYLAMIDE (10000 MW); SODIUM POLYACRYLATE (2500000 MW)

Lidocaine 4 Percent Cream

LIDOCAINE - Lidocaine HCl 4% Cream
SA3, LLC

Disclaimer: Most OTC drugs are not reviewed and approved by FDA, however they may be marketed if they comply with applicable regulations and policies. FDA has not evaluated whether this product complies.

----------

Lidocaine HCl 4% Topical Analgesic Cream

Drug Facts

Active ingredient

Lidocaine HCl 4% w/w

Purpose

Topical Analgesic

Uses

Temporarily relieves pain and itching due to:

- minor cuts
- sunburn
- minor scrapes
- minor burns
- insect bites
- minor skin irritations

Warnings

For external use only.

When using this product

- Avoid contact with the eyes
- Do not use in large quantities, particularly over raw surfaces or blistered areas

Stop use and ask a doctor

- If condition worsens, or if symptoms persist for more than 7 days or clear up and occur again within a few days.
- If allergic reaction occurs or if redness, irritation, swelling, pain or other symptoms begin or increase.

Keep out of reach of children.

If swallowed, get medical help or contact a Poison Control Center right away.

Directions

adults and children 2 years and older | apply externally to the affected area up to 3 to 4 times a day
children under 2 years | ask a doctor

Other information

- May be applied under occlusive dressing.
- Store at 20-25°C (68-77°F); excursions permitted to 15-30°C (59-86°F). See USP Controlled Room Temperature.

Inactive ingredients

Aqua (Deionized Water), Arnica Montana Flower Extract, Boswellia Serrata Extract, Cetearyl Alcohol, Chondroitin Sulfate, Dimethyl Sulfone (MSM), Ethylhexylglycerin, Glucosamine Sulfate, Glycerin, Glyceryl Stearate, C13-14 Isoparaffin, Isostearyl Palmitate, Laureth-7, PEG-100 Stearate, Phenoxyethanol, Polyacrylamide, Propylene Glycol, Sodium Polyacrylate, Stearic Acid, Triethanolamine.

PRINCIPAL DISPLAY PANEL

Lidocaine HCl 4% cream

NDC 69420-6262-1

Topical Analgesic Cream

4.2 OZ (120 g)

SA3, LLC